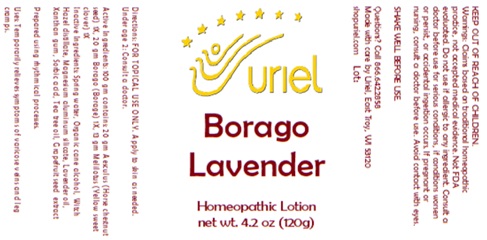 DRUG LABEL: Borago Lavender
NDC: 48951-2144 | Form: LOTION
Manufacturer: Uriel Pharmacy Inc.
Category: homeopathic | Type: HUMAN OTC DRUG LABEL
Date: 20250107

ACTIVE INGREDIENTS: MELILOTUS INDICUS SEED 1 [hp_X]/1 g; HORSE CHESTNUT 1 [hp_X]/1 g; BORAGE 1 [hp_X]/1 g
INACTIVE INGREDIENTS: XANTHAN GUM; SORBIC ACID; TEA TREE OIL; CITRUS PARADISI SEED; ALCOHOL; WATER; MAGNESIUM ALUMINUM SILICATE; LAVENDER OIL; HAMAMELIS VIRGINIANA TOP WATER

Borago Lavender

INDICATIONS AND USAGE

Directions: FOR TOPICAL USE ONLY.

DOSAGE AND ADMINISTRATION

Apply to skin as needed. Under age 2: Consult a doctor.

ACTIVE INGREDIENT

Active Ingredients: 100 gm contains: 20 gm Aesculus (Horse chestnut seed) 1X, 20 gm Borago (Borage) 1X,
12 gm Melilotus (Yellow sweet clover) 1X

INACTIVE INGREDIENT

Inactive Ingredients: Spring water, Organic cane alcohol, Witch Hazel distillate, Magnesium aluminum silicate,
Lavender oil, Xanthan gum, Sorbic acid, Tea tree oil, Grapefruit seed extract

Prepared using rhythmical processes.

PURPOSE

Uses: Temporarily relieves symptoms of varicose veins and leg cramps.

KEEP OUT OF REACH OF CHILDREN.

WARNINGS

Warnings: Claims based on traditional homeopathic practice, not accepted medical evidence. Not FDA evaluated.
Do not use if allergic to any ingredient. Consult a doctor before use for serious conditions, if conditions worsen or persist,
or accidental ingestion occurs. If pregnant or nursing, consult a doctor before use. Avoid contact with eyes.

SHAKE WELL BEFORE USE.

Questions? Call 866.642.2858
Made with care by Uriel, East Troy, WI 53120
shopuriel.com Lot: